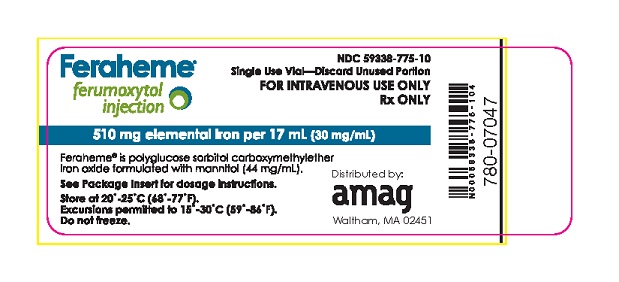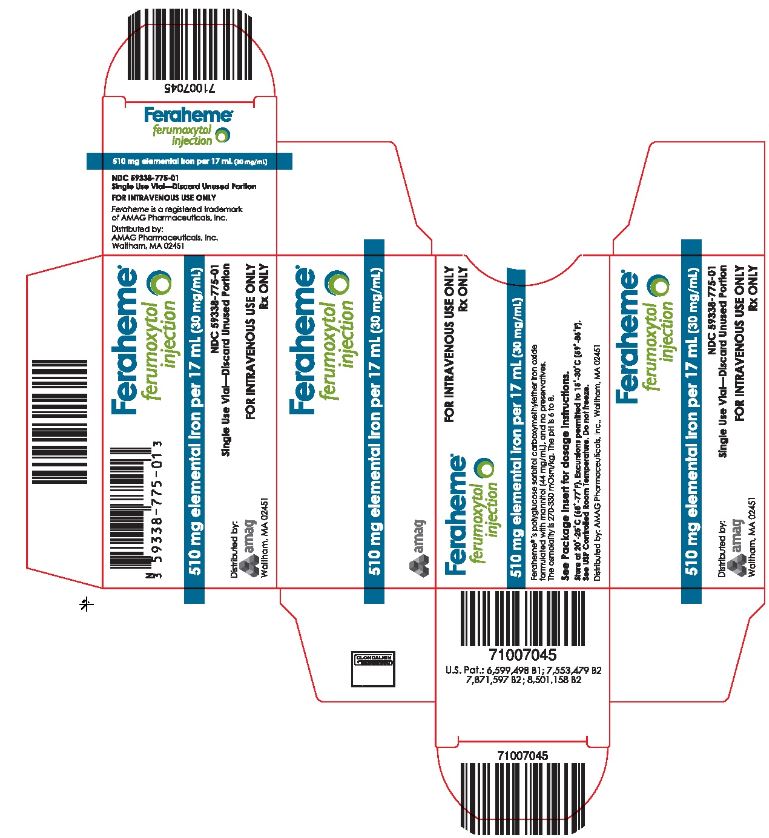 DRUG LABEL: Feraheme
NDC: 59338-775 | Form: INJECTION
Manufacturer: AMAG Pharmaceuticals, Inc.
Category: prescription | Type: HUMAN PRESCRIPTION DRUG LABEL
Date: 20220613

ACTIVE INGREDIENTS: FERUMOXYTOL NON-STOICHIOMETRIC MAGNETITE 510 mg/17 mL
INACTIVE INGREDIENTS: MANNITOL 748 mg/17 mL

HIGHLIGHTS OF PRESCRIBING INFORMATION

These highlights do not include all the information needed to use Feraheme safely and effectively. See full prescribing information for Feraheme.
Feraheme® (ferumoxytol injection), for intravenous use
Initial U.S. Approval: 2009

WARNING: RISK FOR SERIOUS HYPERSENSITIVITY/ANAPHYLAXIS REACTIONS

See full prescribing information for complete boxed warning.

Fatal and serious hypersensitivity reactions including anaphylaxis have occurred in patients receiving Feraheme. Initial symptoms may include hypotension, syncope, unresponsiveness, cardiac/cardiorespiratory arrest.

- Only administer Feraheme as an intravenous infusion over at least 15 minutes and only when personnel and therapies are immediately available for the treatment of anaphylaxis and other hypersensitivity reactions. (5.1)
- Observe for signs or symptoms of hypersensitivity reactions during and for at least 30 minutes following Feraheme infusion including monitoring of blood pressure and pulse during and after Feraheme administration. (5.1)
- Hypersensitivity reactions have occurred in patients in whom a previous Feraheme dose was tolerated. (5.1)

1 INDICATIONS AND USAGE

Feraheme is an iron replacement product indicated for the treatment of iron deficiency anemia (IDA) in adult patients:

- who have intolerance to oral iron or have had unsatisfactory response to oral iron (1) or
- who have chronic kidney disease (CKD). (1)

2 DOSAGE AND ADMINISTRATION

- The recommended dose of Feraheme is an initial 510 mg dose followed by a second 510 mg dose 3 to 8 days later. (2)
- Administer Feraheme as an intravenous infusion in 50-200 mL 0.9% Sodium Chloride Injection, USP or 5% Dextrose Injection, USP over at least 15 minutes (2)

3 DOSAGE FORMS AND STRENGTHS

Injection: 510 mg iron per 17 mL (30 mg per mL) in single-dose vials. (3)

4 CONTRAINDICATIONS

- Known hypersensitivity to Feraheme or any of its components. (4)
- History of allergic reaction to any intravenous iron product. (4)

5 WARNINGS AND PRECAUTIONS

- Greater risk of anaphylaxis in patients with multiple drug allergies. (5.1)
- Hypotension: Feraheme may cause hypotension. Monitor for signs and symptoms of hypotension following each administration of Feraheme. (5.2)
- Iron Overload: Regularly monitor hematologic responses during Feraheme therapy. Do not administer Feraheme to patients with iron overload. (5.3)
- Magnetic Resonance Imaging Test Interference: Feraheme can alter magnetic resonance imaging (MRI) studies. (5.4)

6 ADVERSE REACTIONS

The most common adverse reactions (≥ 2%) are diarrhea, headache, nausea, dizziness, hypotension, constipation, and peripheral edema. (6.1)

To report SUSPECTED ADVERSE REACTIONS with Feraheme, contact AMAG Pharmaceuticals, Inc. at 1-877-411-2510, or FDA at 1-800-FDA-1088 or www.fda.gov/medwatch.

FULL PRESCRIBING INFORMATION

WARNING: RISK FOR SERIOUS HYPERSENSITIVITY/ANAPHYLAXIS REACTIONS

Fatal and serious hypersensitivity reactions including anaphylaxis have occurred in patients receiving Feraheme. Initial symptoms may include hypotension, syncope, unresponsiveness, cardiac/cardiorespiratory arrest.

- Only administer Feraheme as an intravenous infusion over at least 15 minutes and only when personnel and therapies are immediately available for the treatment of anaphylaxis and other hypersensitivity reactions. [see Warnings and Precautions (5.1)].
- Observe for signs or symptoms of hypersensitivity reactions during and for at least 30 minutes following Feraheme infusion including monitoring of blood pressure and pulse during and after Feraheme administration [see Warnings and Precautions (5.1)].
- Hypersensitivity reactions have occurred in patients in whom a previous Feraheme dose was tolerated [see Warnings and Precautions (5.1)].

1 INDICATIONS AND USAGE

Feraheme is indicated for the treatment of iron deficiency anemia (IDA) in adult patients:

- who have intolerance to oral iron or have had unsatisfactory response to oral iron or
- who have chronic kidney disease (CKD).

2 DOSAGE AND ADMINISTRATION

The recommended dose of Feraheme is an initial 510 mg dose followed by a second 510 mg dose 3 to 8 days later. Administer Feraheme as an intravenous infusion in 50-200 mL 0.9% Sodium Chloride Injection, USP or 5% Dextrose Injection, USP over at least 15 minutes. Administer while the patient is in a reclined or semi-reclined position.

Feraheme does not contain antimicrobial preservatives. Discard unused portion. Feraheme, when added to intravenous infusion bags containing either 0.9% Sodium Chloride Injection, USP (normal saline), or 5% Dextrose Injection, USP, at concentrations of 2-8 mg elemental iron per mL, should be used immediately but may be stored at controlled room temperature (25°C ± 2°C) for up to 4 hours or refrigerated (2-8° C) for up to 48 hours.

The dosage is expressed in terms of mg of elemental iron, with each mL of Feraheme containing 30 mg of elemental iron. Evaluate the hematologic response (hemoglobin, ferritin, iron and transferrin saturation) at least one month following the second Feraheme infusion. The recommended Feraheme dose may be readministered to patients with persistent or recurrent iron deficiency anemia.

For patients receiving hemodialysis, administer Feraheme once the blood pressure is stable and the patient has completed at least one hour of hemodialysis. Monitor for signs and symptoms of hypotension following each Feraheme infusion.

Allow at least 30 minutes between administration of Feraheme and administration of other medications that could potentially cause serious hypersensitivity reactions and/or hypotension, such as chemotherapeutic agents or monoclonal antibodies.

Inspect parenteral drug products visually for the absence of particulate matter and discoloration prior to administration.

3 DOSAGE FORMS AND STRENGTHS

Feraheme Injection is available in single-dose vials. Each vial contains 510 mg of elemental iron in 17 mL (30 mg per mL).

4 CONTRAINDICATIONS

Feraheme is contraindicated in patients with:

- Known hypersensitivity to Feraheme or any of its components [see Warnings and Precautions (5.1)]
- History of allergic reaction to any intravenous iron product [see Warnings and Precautions (5.1)]

5 WARNINGS AND PRECAUTIONS

5.1 Serious Hypersensitivity Reactions

Fatal and serious hypersensitivity reactions including anaphylaxis, presenting with cardiac/ cardiorespiratory arrest, clinically significant hypotension, syncope, or unresponsiveness have occurred in patients receiving Feraheme. Other adverse reactions potentially associated with hypersensitivity have occurred (pruritus, rash, urticaria, and wheezing). These reactions have occurred following the first dose or subsequent doses in patients in whom a previous Feraheme dose was tolerated.

Patients with a history of multiple drug allergies may have a greater risk of anaphylaxis with parenteral iron products. Carefully consider the potential risks and benefits before administering Feraheme to these patients.

Only administer Feraheme as an intravenous infusion over at least 15 minutes and only when personnel and therapies are immediately available for the treatment of anaphylaxis and other hypersensitivity reactions. Closely observe patients for signs and symptoms of hypersensitivity including monitoring of blood pressure and pulse during and after Feraheme administration for at least 30 minutes and until clinically stable following completion of each infusion [see Adverse Reactions (6.2)].

In a clinical study in patients with IDA, regardless of etiology, hypersensitivity reactions were reported in 0.4% (4/997) of subjects receiving Feraheme administered as intravenous infusion over at least 15 minutes. These included one patient with severe hypersensitivity reaction and three patients with moderate hypersensitivity reactions.

In clinical studies predominantly in patients with IDA and CKD, serious hypersensitivity reactions were reported in 0.2% (4/1,806) of subjects receiving Feraheme (administered as a rapid intravenous injection – prior method of administration no longer approved). Other adverse reactions potentially associated with hypersensitivity (e.g., pruritus, rash, urticaria or wheezing) were reported in 3.5% (63/1,806) of these subjects.

In the post-marketing experience, fatal and serious anaphylactic type reactions presenting with cardiac/ cardiorespiratory arrest, clinically significant hypotension, syncope, and unresponsiveness have been reported. Elderly patients with multiple or serious co-morbidities who experience hypersensitivity reactions and/or hypotension following administration of Feraheme may have more severe outcomes [see Boxed Warning, Adverse Reactions (6.2) and Use in Specific Populations (8.5)].

5.2 Hypotension

Feraheme may cause clinically significant hypotension.

In a clinical study with Feraheme in patients with IDA, regardless of etiology, moderate hypotension was reported in 0.2% (2/997) of subjects receiving Feraheme administered as intravenous infusion over at least 15 minutes.

In clinical studies in patients with IDA and CKD, hypotension was reported in 1.9% (35/1,806) of subjects, including three patients with serious hypotensive reactions, who had received Feraheme as a rapid intravenous injection (prior method of administration no longer approved).

Hypotension has also been reported in the post-marketing experience [see Adverse Reactions (6.2)]. Monitor patients for signs and symptoms of hypotension following each Feraheme administration [see Dosage and Administration (2) and Warnings and Precautions (5.1)].

5.3 Iron Overload

Excessive therapy with parenteral iron can lead to excess storage of iron with the possibility of iatrogenic hemosiderosis. Regularly monitor the hematologic response during parenteral iron therapy [see Dosage and Administration (2)]. Do not administer Feraheme to patients with iron overload.

In the 24 hours following administration of Feraheme, laboratory assays may overestimate serum iron and transferrin bound iron by also measuring the iron in the Feraheme complex.

5.4 Magnetic Resonance (MR) Imaging Test Interference

Administration of Feraheme may transiently affect the diagnostic ability of MR imaging. Conduct anticipated MR imaging studies prior to the administration of Feraheme. Alteration of MR imaging studies may persist for up to 3 months following the last Feraheme dose. If MR imaging is required within 3 months after Feraheme administration, use T1- or proton density-weighted MR pulse sequences to minimize the Feraheme effects; MR imaging using T2-weighted pulse sequences should not be performed earlier than 4 weeks after the administration of Feraheme. Maximum alteration of vascular MR imaging is anticipated to be evident for 1 – 2 days following Feraheme administration [see Clinical Pharmacology (12.3)].

Feraheme will not interfere with X-ray, computed tomography (CT), positron emission tomography (PET), single photon emission computed tomography (SPECT), ultrasound or nuclear medicine imaging.

6 ADVERSE REACTIONS

The following clinically significant adverse reactions are described elsewhere in the labeling:

- Serious Hypersensitivity Reactions [see Warnings and Precautions (5.1)]
- Hypotension [see Warnings and Precautions (5.2)]
- Iron Overload [see Warnings and Precautions (5.3)]
- Magnetic Resonance (MR) Imaging Test Interference [see Warnings and Precautions (5.4)]

6.1 Clinical Trials Experience

Because clinical trials are conducted under widely varying conditions, adverse reaction rates observed in the clinical trials of a drug cannot be directly compared to rates in the clinical trials of another drug and may not reflect the rates observed in practice.

In clinical studies, 3,968 subjects were exposed to Feraheme. Of these subjects 31% were male and the median age was 54 years (range of 18 to 96 years).

The data described below reflect exposure to Feraheme in 997 patients exposed to a 1.02 g course of ferumoxytol administered as two 510 mg intravenous (IV) doses: 992 subjects (99.5%) received at least 1 complete dose of ferumoxytol and 946 subjects (94.9%) received 2 complete doses. The mean cumulative IV Iron exposure was 993.80 ±119.085 mg.

The safety of Feraheme was studied in a randomized, multicenter, double-blind clinical trial in patients with IDA (IDA Trial 3), [see Clinical Studies (14.1)]. In this trial, patients were randomized to two intravenous infusions of 510 mg (1.02 g) of Feraheme (n=997), or two intravenous infusions of 750 mg (1.500 g) of ferric carboxymaltose (FCM) (n=1000). Both intravenous irons were infused over a period of at least 15 minutes. Most patients received their second infusion of Feraheme and FCM 7(+1) days after Dose 1.

The mean (SD) age of the study population (N=1997) was 55.2 (17.16) years. The majority of patients were female (76.1%), white (71.4%) and non-Hispanic (81.8%). The mean (SD) hemoglobin at baseline for all patients was 10.4 (1.5) g/dl.

Serious adverse events were reported in 3.6% (71/1997) of ferumoxytol- and FCM- treated patients. The most common (≥2 subjects) serious AEs reported in Feraheme-treated patients were syncope, gastroenteritis, seizure, pneumonia, hemorrhagic anemia, and acute kidney injury. In FCM-treated patients the most common (≥2 subjects) serious AEs were syncope, cardiac failure congestive, angina pectoris, and atrial fibrillation.

Adverse reactions related to Feraheme and reported by ≥1% of Feraheme-treated patients in IDA Trial 3 are listed in Table 1.

Table 1: Adverse Reactions to Feraheme Reported in ≥1% of IDA Patients in IDA Trial 3
Adverse Reactions | Feraheme 2 x 510 mg (N = 997) % | Ferric Carboxymaltose 2 x 750 mg (N = 1000) %
Headache | 3.4 | 3.1
Nausea | 1.8 | 3.4
Dizziness | 1.5 | 1.6
Fatigue | 1.5 | 1.2
Diarrhea | 1 | 0.8
Back Pain | 1 | 0.4

In IDA Trial 3, adverse reactions leading to treatment discontinuation and occurring in ≥ 2 Feraheme-treated patients included arthralgia (0.3%), dyspnea (0.3%), flushing (0.2%), chest discomfort (0.2%), chest pain (0.2%), nausea (0.2%), back pain (0.2%), dizziness (0.2%) and headache (0.2%).

Across two clinical trials in patients with IDA (IDA Trial 1 and 2), [see Clinical Studies (14.1)], patients were randomized to: two injections (rapid intravenous injection - prior method of administration no longer approved) of 510 mg of Feraheme (n=1,014), placebo (n=200), or five injections/infusions of 200 mg of iron sucrose (n=199). Most patients received their second Feraheme injection 3 to 8 days after the first injection. Adverse reactions related to Feraheme and reported by ≥ 1% of Feraheme-treated patients in these trials were similar to those seen in Trial 3.

In Trials 1 and 2, adverse reactions leading to treatment discontinuation and occurring in ≥ 2 Feraheme-treated patients included hypersensitivity (0.6%), hypotension (0.3%), and rash (0.2%).

In addition, a total of 634 subjects enrolled in and completed participation in a Phase 3 open label extension study. Of these, 337 subjects met IDA treatment criteria and received Feraheme. Adverse reactions following this repeat Feraheme dosing were generally similar in type and frequency to those observed after the first two intravenous injections.

Across three randomized clinical trials in patients with IDA and CKD (CKD Trials 1, 2, and 3), [see Clinical Studies (14.2)], a total of 605 patients were exposed to two injections of 510 mg of Feraheme and a total of 280 patients were exposed to 200 mg/day of oral iron for 21 days. Most patients received their second Feraheme injection 3 to 8 days after the first injection.

Adverse reactions related to Feraheme and reported by ≥ 1% of Feraheme-treated patients in the CKD randomized clinical trials are listed in Table 2 . Diarrhea (4%), constipation (2.1%) and hypertension (1%) have also been reported in Feraheme-treated patients.

Table 2: Adverse Reactions to Feraheme Reported in ≥1% of Patients with IDA and CKD Trials 1, 2 and 3
Adverse Reactions | Feraheme 2 x 510 mg (n = 605) % | Oral Iron (n = 280) %
Nausea | 3.1 | 7.5
Dizziness | 2.6 | 1.8
Hypotension | 2.5 | 0.4
Peripheral Edema | 2 | 3.2
Headache | 1.8 | 2.1
Edema | 1.5 | 1.4
Vomiting | 1.5 | 5
Abdominal Pain | 1.3 | 1.4
Chest Pain | 1.3 | 0.7
Cough | 1.3 | 1.4
Pruritus | 1.2 | 0.4
Pyrexia | 1 | 0.7
Back Pain | 1 | 0
Muscle Spasms | 1 | 1.4
Dyspnea | 1 | 1.1
Rash | 1 | 0.4

In these clinical trials in patients with IDA and CKD, adverse reactions leading to treatment discontinuation and occurring in ≥ 2 Feraheme-treated patients included hypotension (0.4%), chest pain (0.3%), and dizziness (0.3%).

Following completion of the controlled phase of the trials, 69 patients received two additional 510 mg intravenous injections of Feraheme (for a total cumulative dose of 2.04 g). Adverse reactions following this repeat Feraheme dosing were similar in character and frequency to those observed following the first two intravenous injections.

6.2 Postmarketing Experience

Because adverse reactions are reported voluntarily from a population of uncertain size, it is not always possible to reliably estimate their frequency or establish a causal relationship to drug exposure.

The following serious adverse reactions have been reported from the post-marketing experience with Feraheme: fatal, life-threatening, and serious anaphylactic-type reactions, acute myocardial ischemia with or without myocardial infarction or with in-stent thrombosis in the context of a hypersensitivity reaction, cardiac/cardiorespiratory arrest, clinically significant hypotension, syncope, unresponsiveness, loss of consciousness, tachycardia/rhythm abnormalities, angioedema, ischemic myocardial events, congestive heart failure, pulse absent, and cyanosis. These adverse reactions have usually occurred within 30 minutes after the administration of Feraheme. Reactions have occurred following the first dose or subsequent doses of Feraheme.

7 DRUG INTERACTIONS

Drug-drug interaction studies with Feraheme were not conducted. Feraheme may reduce the absorption of concomitantly administered oral iron preparations.

8 USE IN SPECIFIC POPULATIONS

8.1 Pregnancy

Risk Summary

Limited available data with ferumoxytol use in pregnant women are insufficient to inform a drug associated risk of adverse developmental outcomes. There are risks to the mother and fetus associated with untreated iron deficiency anemia (IDA) in pregnancy as well as risks to the fetus associated with maternal severe hypersensitivity reactions (see Clinical Considerations). In animal studies, administration of ferumoxytol to pregnant rabbits during organogenesis caused adverse developmental outcomes including fetal malformations and decreased fetal weights at maternally toxic doses of 6 times the estimated human daily dose.

The estimated background risk of major birth defects and miscarriage for the indicated populations is unknown. All pregnancies have a background risk of birth defect, loss, or other adverse outcomes. In the U.S. general population, the estimated background risk of major birth defect and miscarriage in clinically recognized pregnancies is 2-4% and 15-20%, respectively.

Clinical Considerations

Disease-associated maternal and/or embryo/fetal risk

Untreated iron deficiency anemia (IDA) in pregnancy is associated with adverse maternal outcomes such as post-partum anemia. Adverse pregnancy outcomes associated with IDA include increased risk for preterm delivery and low birth weight.

Fetal/Neonatal adverse reactions

Severe adverse reactions including circulatory failure (severe hypotension, shock including in the context of anaphylactic reaction) may occur in pregnant women with parenteral iron products (such as Feraheme) which may cause fetal bradycardia, especially during the second and third trimester.

Data

Animal Data

Administration of ferumoxytol during organogenesis, at doses of 31.6 mg Fe/kg/day in rats and 16.5 mg Fe/kg/day in rabbits, did not result in maternal or fetal effects. These doses are approximately 2 times the estimated human daily dose based on body surface area. In rats, administration of ferumoxytol during organogenesis at a maternally toxic dose of 100 mg Fe/kg/day, approximately 6 times the estimated human daily dose based on body surface area, caused a decrease in fetal weights. In rabbits, administration of ferumoxytol during organogenesis at a maternally toxic dose of 45 mg Fe/kg/day, approximately 6 times the estimated human daily dose based on body surface area, was associated with external and soft tissue fetal malformations and decreased fetal weights.

8.2 Lactation

Risk Summary

There are no data on the presence of ferumoxytol in human milk, the effects on the breastfed child, or the effects on milk production. Ferumoxytol has been detected in the milk of lactating rats. However, due to species-specific differences in lactation physiology, the clinical relevance of these data are not clear. The developmental and health benefits of breastfeeding should be considered along with the mother’s clinical need for Feraheme and any potential adverse effects on the breastfed child from Feraheme or from the underlying maternal condition.

8.4 Pediatric Use

The safety and effectiveness of Feraheme in pediatric patients (less than 18 years old) have not been established.

8.5 Geriatric Use

In controlled clinical trials, 833 patients ≥ 65 years of age were treated with Feraheme. No overall differences in safety and efficacy were observed between older and younger patients in these trials, but greater sensitivity of older individuals cannot be ruled out. In general, dose administration to an elderly patient should be cautious, reflecting the greater frequency of decreased hepatic, renal, or cardiac function, and of concomitant disease or other drug therapy. Elderly patients with multiple or serious co-morbidities who experience hypersensitivity reactions and/or hypotension following administration of Feraheme may have more severe outcomes. The potential risks and benefits of Feraheme administration should be carefully considered in these patients [see Dosage and Administration (2), Warnings and Precautions (5.1), and Clinical Studies (14)].

10 OVERDOSAGE

Limited data are available regarding overdosage of Feraheme in humans.

Excessive dosages of Feraheme may lead to accumulation of iron in storage sites potentially leading to hemosiderosis. Do not administer Feraheme to patients with iron overload [Warnings and Precautions (5.3)].
Feraheme is not removed by hemodialysis.

11 DESCRIPTION

Feraheme is an iron replacement product containing ferumoxytol for intravenous infusion. Ferumoxytol is a non-stoichiometric magnetite (superparamagnetic iron oxide) coated with polyglucose sorbitol carboxymethylether. The overall colloidal particle size is 17-31 nm in diameter. The chemical formula of Feraheme is Fe5874O8752-C11719H18682O9933Na414 with an apparent molecular weight of 750 kDa.

Feraheme Injection is a sterile aqueous colloidal product that is formulated with mannitol. It is a black to reddish brown liquid, and is provided in single-dose vials containing 510 mg of elemental iron. Each mL of the sterile colloidal solution of Feraheme Injection contains 30 mg of elemental iron, 30 mg polyglucose sorbitol carboxymethylether, and 44 mg of mannitol. The formulation is isotonic with an osmolality of 270-330 mOsm/kg. The product contains no preservatives, and has a pH of 6 to 8.

12 CLINICAL PHARMACOLOGY

12.1 Mechanism of Action

Feraheme consists of a superparamagnetic iron oxide that is coated with a carbohydrate shell, which helps to isolate the bioactive iron from plasma components until the iron-carbohydrate complex enters the reticuloendothelial system macrophages of the liver, spleen and bone marrow. The iron is released from the iron-carbohydrate complex within vesicles in the macrophages. Iron then either enters the intracellular storage iron pool (e.g., ferritin) or is transferred to plasma transferrin for transport to erythroid precursor cells for incorporation into hemoglobin.

12.2 Pharmacodynamics

Cardiac Electrophysiology
In a randomized, positive- and placebo-controlled, parallel-group study, healthy subjects received a supratherapeutic regimen of Feraheme (1.02 g given as two 510 mg doses within 24 hours), placebo or a single dose of 400 mg moxifloxacin (positive control). Results demonstrated no effect of Feraheme on QT interval durations. No clinically meaningful effect of Feraheme on heart rate was observed.

12.3 Pharmacokinetics

The pharmacokinetic (PK) behavior of Feraheme has been examined in healthy subjects and in patients with CKD stage 5D on hemodialysis. Feraheme exhibited dose-dependent, capacity-limited elimination from plasma with a half-life of approximately 15 hours in humans. The clearance (CL) was decreased by increasing the dose of Feraheme. Volume of distribution (Vd) was consistent with plasma volume, and the mean maximum observed plasma concentration (Cmax) and terminal half-life (t1/2) values increased with dose. The estimated values of CL and Vd following two 510 mg doses of Feraheme administered intravenously within 24 hours were 69.1 mL/hr and 3.16 L, respectively. The Cmax and time of maximum concentration (tmax) were 206 mcg/mL and 0.32 hr, respectively. Rate of infusion had no influence on Feraheme PK parameters. No gender differences in Feraheme PK parameters were observed. Feraheme is not removed by hemodialysis.

13 NONCLINICAL TOXICOLOGY

13.1 Carcinogenesis, Mutagenesis, Impairment of Fertility

Ferumoxytol was not tested for carcinogenic effects. In standard genotoxicity tests, ferumoxytol showed no evidence of mutagenic activity in an in vitro Ames test or clastogenic activity in either an in vitro chromosomal aberration assay or an in vivo micronucleus assay.

No adverse effects on fertility or general reproductive performance were noted in animal studies. Ferumoxytol had no effect on male or female fertility or general reproductive function in rats. In a pre and postnatal development study in rats, intravenous administration of ferumoxytol from gestation day 6 until lactation day 20 at doses up to 60 mg/kg/day (approximately 3 times the daily human dose based on body surface area comparisons assuming a 60-kg person) had no effect on maternal delivery or numbers of liveborn offspring. Male offspring (F1) of pregnant rats (F0) administered ferumoxytol at a dose of 60 mg/kg/day had delayed sexual maturation and decreased reproductive competence. Female offspring (F1) of pregnant rats (F0) administered ferumoxytol at doses of 30 mg/kg/day or 60 mg/kg/day had delayed sexual maturation and decreased reproductive competence. Doses of 30 mg/kg/day and 60 mg/kg/day are approximately 2 and 3 times the daily human dose based on body surface area comparisons assuming a 60-kg person, respectively.

14 CLINICAL STUDIES

14.1 Iron Deficiency Anemia in Patients Who Are Intolerant to Oral Iron or Have Had Unsatisfactory Response to Oral Iron

IDA-301 Trial (referred to as IDA Trial 1) (NCT 01114139), IDA-302 Trial (referred to as IDA Trial 2) (NCT 01114204) and IDA-304 Trial (referred to as IDA Trial 3) (NCT 02694978)

The safety and efficacy of Feraheme in patients with iron deficiency anemia, regardless of etiology and a history of unsatisfactory oral iron therapy or in whom oral iron could not be used, were assessed in two randomized, controlled clinical trials (IDA Trial 1 and 2) with Feraheme administered as a rapid intravenous injection (prior method of administration no longer approved). In IDA Trial 1, patients were randomized to treatment with Feraheme or placebo. In IDA Trial 2, patients were randomized to treatment with Feraheme or iron sucrose. Feraheme (510 mg) and placebo were administered as two intravenous single dose injections over 3-8 days, and iron sucrose (200 mg) was administered as 5 intravenous injections or infusions over a period of 14 days.

In IDA Trial 1, the mean age of patients was 45 years (range, 18 to 91); 89% were female; 56% were Caucasian, 25% were Black, 16% were Asian, and 3% were other races.

In IDA Trial 2, the mean age of patients was 48 years (range, 18 to 89); 83% were female; 84% were Caucasian, 11% were Asian, 1% were Black, and 4% were other races.

Table 3 shows changes from baseline to Week 5 in hemoglobin and transferrin saturation in IDA Trial 1 and 2.

Table 3: Changes from Baseline to Week 5 in Hemoglobin (Hgb) and Transferrin Saturation in IDA Trial 1 and 2 (Intent to Treat Population)
ENDPOINT | IDA Trial 1 |  | IDA Trial 2
ENDPOINT | Feraheme N = 608 | Placebo N = 200 | Feraheme N = 406 | Iron Sucrose N = 199
Baseline Hgb mean (SD), g/dL | 8.9 (0.9) | 8.8 (0.9) | 8.9 (0.9) | 8.8 (1.0)
Proportion of patients with Hgb Increase of ≥2.0 g/dL at any time from Baseline to Week 5, % | 81.1 | 5.5 | 84.0 | 81.4
Treatment Difference (%, 95% CI) | 75.6* (71.2, 80.0) |  | 2.6 (-3.9, 9.1)
Mean change in Hgb from Baseline to Week 5 mean (SD), g/dL | 2.6 (1.5) | 0.1 (0.9) | 2.9 (1.6) | 2.7 (1.3)
Proportion of patients with Hgb ≥12 g/dL at any time from Baseline to Week 5, % | 50.5 | 3.0 | 66.7 | 48.2
Baseline TSAT mean (SD) , % | 7.0 (12.9) | 5.4 (4.9) | 6.1 (9.9) | 5.5 (10.3)
Mean change in TSAT from Baseline to Week 5 mean (SD), % | 11.4 (15.1) | 0.4 (5.8) | 15.7 (16.8) | 11.9 (14.4)
* p≤0.001 for main efficacy endpoint

In IDA Trial 1, fatigue-related symptoms and impacts were assessed using a patient reported outcome instrument, FACIT-Fatigue (score range from 0 to 52 with higher scores indicating less fatigue). After 5 weeks, Feraheme-treated patients reported greater improvement from baseline in the fatigue score (+11.7 ± 11.73 points) than did patients in the placebo arm (+6.8 ± 9.51 points) with a treatment difference of 4.9 (95% CI: 3.08-6.71) points.

The safety of Feraheme in IDA patients with a history of unsatisfactory oral iron therapy or in whom oral iron could not be used was also assessed in another randomized, multicenter, double-blind safety clinical trial (IDA Trial 3). Patients were randomized in a 1:1 ratio to either two infusions of 510 mg (1.020 g) of Feraheme (n=997) or two infusions of 750 mg (1.500 g) of ferric carboxymaltose (FCM) (n=1000). Both IV irons were infused over a period of at least 15 minutes. Most patients received their second infusion of Feraheme or FCM 7(+1) days after the first infusion. This study included patients with any etiology of IDA including CKD excluding dialysis-dependent CKD.

In IDA Trial 3, the mean age of patients was 55 years (range, 18 to 96); 76% were female; 71% were Caucasian, 24% were Black, 3% were Asian, and 2% were other races.

The study met the primary endpoint to demonstrate non-inferiority to FCM with respect to the percentage of patients who experienced moderate-to-severe hypersensitivity reactions (including anaphylaxis) or moderate-to-severe hypotension (Feraheme: 0.6%; FCM: 0.7%; treatment difference: -0.1%; exact 95% confidence interval: -0.91% to +0.70%).

Table 4 shows the mean increase from baseline to week 5 in hemoglobin (Hgb) per treatment (Feraheme 2 x 510 mg; FCM 2 x 750 mg) and per gram of iron administered (Feraheme 1.020 g; FCM 1.500 g) in IDA Trial 3.

Table 4: Summary of Hemoglobin (Hgb) Changes per Treatment and per Gram of Iron Administered From Baseline to Week 5 (Intent to Treat Population) in IDA Trial 3
ENDPOINT | Feraheme 2 x 510mg N = 997 | Ferric Carboxymaltose (FCM) 2 x 750mg N = 1000
Baseline Hgb mean (SD); g/dL | 10.42 (1.48) | 10.39 (1.46)
Mean change in Hgb from Baseline to Week 5 per Gram of Iron Administered mean (SD); g/dL | 1.35 (1.35) | 1.10 (1.05)
Treatment Difference Per Gram of Irona (%, 95%CI) | 0.26 (0.17, 0.36)
Mean change in Hgb from Baseline to Week 5 mean (SD); g/dL | 1.38 (1.35) | 1.63 (1.54)
Treatment Differencea (%, 95% CI) | -0.24 (-0.35, -0.13)
aAdjusted for difference in baseline Hgb

In IDA Trial 3, the incidence of severe hypophosphatemia (defined by blood phosphorous of <0.6 mmol/L at week 2) in the patients receiving Feraheme (0.4% of patients) was less than those receiving FCM (38.7% of patients).

14.2 Iron Deficiency Anemia in Patients with Chronic Kidney Disease

Trial 62745-7 (referred to as CKD Trial 1) (NCT 00255437), Trial 62745-6 (referred to as CKD Trial 2) (NCT 00255424), and Trial 62745-5 (referred to as CKD Trial 3) (NCT 00233597).

The safety and efficacy of Feraheme for the episodic treatment of iron deficiency anemia in patients with CKD were assessed in three randomized, open-label, controlled clinical trials (CKD Trial 1, 2 and 3) where Feraheme was administered as a rapid intravenous injection (prior method of administration - no longer approved). These trials also included an uncontrolled, follow-up phase in which patients with persistent iron deficiency anemia could receive two additional 510 mg intravenous injections of Feraheme. The major efficacy results from the controlled phase of each study are shown in Table 5.

In all three trials, patients with CKD and iron deficiency anemia were randomized to treatment with Feraheme or oral iron. Feraheme was administered as two 510 mg undiluted intravenous injections and oral iron (ferrous fumarate) was administered as a total daily dose of 200 mg elemental iron daily for 21 days. The major trial outcomes assessed the change in hemoglobin from baseline to Day 35. CKD Trial 1 and 2 enrolled patients with non-dialysis dependent CKD and CKD Trial 3 enrolled patients who were undergoing hemodialysis.

In CKD Trial 1, the mean age of patients was 66 years (range, 23 to 95); 60% were female; 65% were Caucasian, 32% were Black, and 2% were other races. In the Feraheme and oral iron groups, 42% and 44% of patients, respectively, were receiving erythropoiesis stimulating agents (ESAs) at baseline.

In CKD Trial 2, the mean age of patients was 65 years (range, 31 to 96); 61% were female; 58% were Caucasian, 35% were Black, and 7% were other races. In the Feraheme and oral iron groups, 36% and 43% of patients, respectively, were receiving ESAs at baseline.

In CKD Trial 3, the mean age of patients was 60 years (range, 24 to 87); 43% were female; 34% were Caucasian, 59% were Black, and 7% were other races. All patients were receiving ESAs.

Table 5 shows the Baseline and mean change to Day 35 in hemoglobin (Hgb, g/dL), transferrin saturation (TSAT, %) and ferritin (ng/mL) in each treatment group for Trial 1, 2, and 3.

Table 5: Changes from Baseline to Day 35 in Hemoglobin (Hgb), Transferrin Saturation and Ferritin (Intent to Treat Population) in CKD Trials 1, 2 and 3
ENDPOINT | CKD Trial 1 Non-Dialysis |  | CKD Trial 2 Non-Dialysis |  | CKD Trial 3 Dialysis
ENDPOINT | Feraheme N = 226 | Oral Iron N = 77 | Feraheme N = 228 | Oral Iron N = 76 | Feraheme N = 114 | Oral Iron N = 116
Baseline Hgb mean (SD), g/dL | 9.9 (0.8) | 9.9 (0.7) | 10.0 (0.7) | 10.0 (0.8) | 10.6 (0.7) | 10.7(0.6)
Hgb change from Baseline at Day 35 mean (SD), g/dL | 1.2* (1.3) | 0.5(1.0) | 0.8* (1.2) | 0.2 (1.0) | 1.0*(1.1) | 0.5 (1.1)
Baseline TSAT mean (SD), % | 9.8 (5.4) | 10.4 (5.2) | 11.3 (6.1) | 10.1 (5.5) | 15.7(7.2) | 15.9 (6.3)
TSAT change from Baseline at Day 35 mean (SD), % | 9.2 (9.4) | 0.3 (4.7) | 9.8 (9.2) | 1.3 (6.4) | 6.4 (12.6) | 0.6 (8.3)
Baseline ferritin mean (SD), ng/mL | 123.7 (125.4) | 146.2 (136.3) | 146.1 (173.6) | 143.5 (144.9) | 340.5 (159.1) | 357.6 (171.7)
Ferritin change from Baseline at Day 35 mean (SD), ng/mL | 300.7 (214.9) | 0.3 (82.0) | 381.7 (278.6) | 6.9 (60.1) | 233.9 (207.0) | -59.2 (106.2)
* p≤0.001 for main efficacy endpoint

Following completion of the controlled phase of each of the Phase 3 trials, patients who were iron deficient and anemic could receive two additional 510 mg intravenous injections of Feraheme for a total cumulative dose of 2.04 g. Overall, 69 patients received two additional 510 mg intravenous injections of Feraheme, and on Day 35 following these additional injections, the majority of these patients (70%) experienced an increase in hemoglobin and iron parameters (TSAT and ferritin). The mean change (±SD) in hemoglobin level from the retreatment baseline for patients with an increase in hemoglobin was 0.86 (± 0.68) g/dL and was 0.5 (± 0.8) g/dL for all patients.

In a randomized, controlled clinical trial of 162 IDA patients with CKD (92 Non-Dialysis and 70 on Dialysis), mean change in hemoglobin from Baseline to Week 5 was 0.71 ±1.03 g/dL for Feraheme-treated patients and 0.61 ±0.97 g/dL for iron sucrose-treated patients.

16 HOW SUPPLIED/STORAGE AND HANDLING

16.1 How Supplied

Feraheme is available in single-dose vials in the following package sizes (Table 6).

Table 6: Feraheme Packaging Description
NDC Code | Dose / Total volume per vial | Vials / Carton
NDC 59338-775-01 | 510 mg/ 17 mL | 1
NDC 59338-775-10 | 510 mg/ 17 mL | 10

16.2 Stability and Storage

Store at 20° to 25°C (68° to 77°F). Excursions permitted to 15° – 30°C (59° – 86°F) [see USP controlled room temperature].

17 PATIENT COUNSELING INFORMATION

Advise the patient to read the FDA-approved patient labeling (Patient Information).

Prior History of Allergies to Parenteral Iron Products

Question patients regarding any prior history of allergies to parenteral iron products [see Warnings and Precautions (5.1)].

Hypersensitivity Reactions

Advise patients to immediately report any symptoms of hypersensitivity that may develop during and following Feraheme administration, such as rash, itching, dizziness, light-headedness, swelling, and breathing problems [see Warnings and Precautions (5.1)].

U.S Patents: 6,599,498 B1; 7,553,479 B2; 7,871,597 B2; 8,501,158 B2; 8,591,864 B2; 8,926,947 B2

Distributed by: AMAG Pharmaceuticals, Inc. Waltham, MA 02451

Patient Information
Feraheme (FER-uh-heem)
(ferumoxytol injection)

What is the most important information I should know about Feraheme?

Feraheme may cause serious side effects including:

- Serious allergic reactions that can lead to death. Serious allergic reactions have happened in people after receiving the first dose of Feraheme or after receiving additional doses in people who did not previously have an allergic reaction. If you have a history of allergies to many different medicines, you may have an increased risk of serious allergic reactions to Feraheme. Tell your healthcare provider or get medical help right away if you get any of these signs or symptoms:
  - rash
  - itching
  - dizziness or lightheadedness
  - swelling of the tongue or throat
  - wheezing or trouble breathing

See “What are the possible side effects of Feraheme?” for more information about side effects.

What is Feraheme?

Feraheme is a prescription medicine used to treat iron deficiency anemia in adults who have:

- intolerance to oral iron or who have not responded well to treatment with oral iron or
- chronic kidney disease (CKD)

It is not known if Feraheme is safe and effective in children less than 18 years of age.

Who should not receive Feraheme?

Do not receive Feraheme if you:

- are allergic to Feraheme or any of the ingredients in Feraheme. See the end of this leaflet for a complete list of ingredients in Feraheme.
- have had an allergic reaction to any iron medicine given into your vein by intravenous (IV) infusion.

Before receiving Feraheme, tell your healthcare provider about all of your medical conditions, including if you:

- have allergies to many different medicines
- have iron overload
- have low blood pressure (hypotension).
- are pregnant or plan to become pregnant. It is not known if Feraheme will harm your unborn baby.
- are breastfeeding or plan to breastfeed. It is not known if Feraheme passes into your breast milk. You and your healthcare provider should decide if you will receive Feraheme or breastfeed.

Tell your healthcare provider about all the medicines you take, including prescription and over-the-counter medicines, vitamins, and herbal supplements.

How will I receive Feraheme?

- Feraheme will be given to you into your vein by intravenous (IV) infusion over at least 15 minutes by your healthcare provider. You will receive Feraheme in 2 doses 3 to 8 days apart.
- Your healthcare provider will watch you during and for at least 30 minutes after you receive Feraheme.

What are the possible side effects of Feraheme?

Feraheme can cause serious side effects, including:

- See “What is the most important information I should know about Feraheme?”
- Low blood pressure (hypotension) is a common side effect of Feraheme and can sometimes be serious. Your healthcare provider will check you for signs and symptoms of hypotension after each Feraheme infusion.
- Iron overload. Your healthcare provider will do blood tests to check your iron levels during treatment with Feraheme.

The most common side effects of Feraheme include: diarrhea, headache, nausea, dizziness, constipation, and swelling of your legs, feet, arms, or hands.

These are not all of the possible side effects of Feraheme. Call your doctor for medical advice about side effects. You may report side effects to FDA at 1-800-FDA-1088.

General information about the safe and effective use of Feraheme.

Medicines are sometimes prescribed for purposes other than those listed in a Patient Information leaflet. If you would like more information, talk to your healthcare provider. You can ask your pharmacist or healthcare provider for information about Feraheme that is written for health professionals.

What are the ingredients in Feraheme?

Active ingredient: ferumoxytol

Inactive ingredient: mannitol

Distributed by: AMAG Pharmaceuticals, Inc. Waltham, MA 02451
For more information, go to www.feraheme.com or call 1--877-411-2510.

This Patient Information has been approved by the U.S. Food and Drug Administration. Revised: 02/2018

PACKAGE LABEL

Package Label - Principal Display Panel – 17 mL Vial, Feraheme Injection

PACKAGE LABEL

Package Label - Principal Display Panel – Carton for Single Use Vial, Feraheme Injection